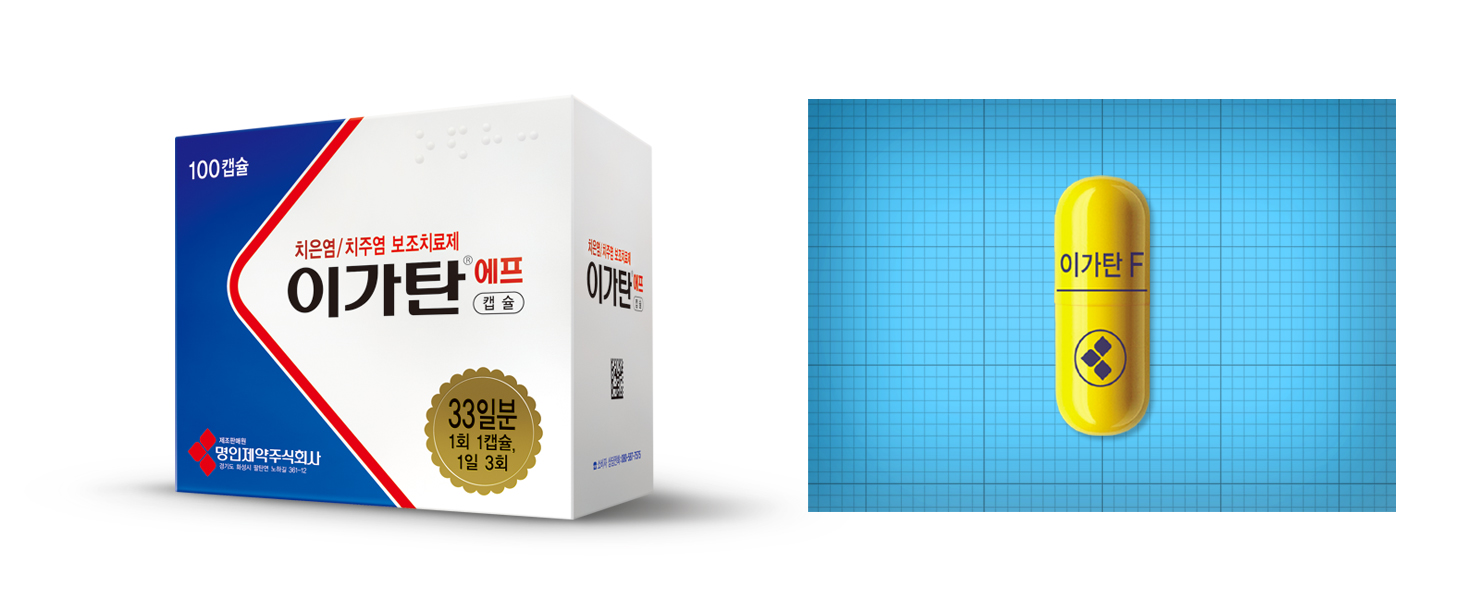 DRUG LABEL: IGATAN F
NDC: 72689-0027 | Form: CAPSULE
Manufacturer: OASIS TRADING
Category: otc | Type: HUMAN OTC DRUG LABEL
Date: 20181213

ACTIVE INGREDIENTS: ASCORBIC ACID 156 mg/1 1; .ALPHA.-TOCOPHEROL ACETATE 10 mg/1 1; CARBAZOCHROME 2 mg/1 1
INACTIVE INGREDIENTS: LACTOSE MONOHYDRATE; SILICON DIOXIDE; SODIUM STARCH GLYCOLATE TYPE A CORN; MICROCRYSTALLINE CELLULOSE; MAGNESIUM STEARATE; STARCH, CORN

ACTIVE INGREDIENT

COATED ASCORBIC ACID, TOCOPHEROL ACETATE, CARBAZOCHROME, LYSOZYME CHLORIDE

PURPOSE

Preventing further damage to the gum tissue

Anti-inflammatory and Hemostatic action

Synergistic effect of periodontal disease treatment

Keep out of reach of children

INDICATIONS AND USAGE

Adults: Take one capsule three times a day after meals.

WARNINGS

Please refer to the leaflet enclosed.

INACTIVE INGREDIENT

Corn starch, Lactose hydrate, Microcrystalline cellulose, Sodium starch glycolate, Colloidal silicon dioxide, Magnesium stearate, Capsule, Sunset yellow FCF, Quinoline yellow WS

DOSAGE AND ADMINISTRATION

For oral use only